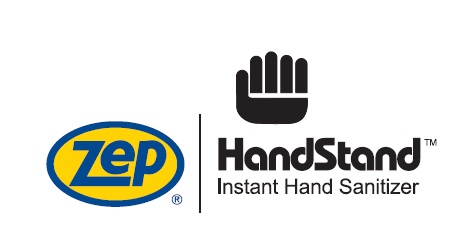 DRUG LABEL: Zep Handstand Instant Hand Sanitizer
NDC: 66949-906 | Form: LIQUID
Manufacturer: Zep Inc.
Category: otc | Type: HUMAN OTC DRUG LABEL
Date: 20251226

ACTIVE INGREDIENTS: ALCOHOL 62 g/100 mL
INACTIVE INGREDIENTS: GLYCERIN; .ALPHA.-TOCOPHEROL; AMINOMETHYLPROPANOL; ISOPROPYL MYRISTATE; ALOE VERA LEAF; CARBOMER HOMOPOLYMER, UNSPECIFIED TYPE; PROPYLENE GLYCOL; WATER

66949-906 / 0906 Handstand Instant Hand Sanitizer

Active Ingredient

Ethyl Alcohol 62%

Purpose

Antiseptic Agent

Uses

Hand sanitizer to help reduce bacteria on the skin that could cause disease. Recommended for repeated use.

Warnings

Flammable. Keep away from heat or flame.

For external use only.

Do not use in the eyes. In case of contact, rinse thoroughly.

Stop use and ask a doctor if irritation and redness appears and lasts.

Keep out of reach of children. If swallowed, contact a physician or poison control center.

Directions

- To decrease bacteria on skin, apply a small amount to palm. Briskly rub, covering hands with product until dry.
- Children should be supervised when using this product.

Inactive Ingredients

Water, Glycerin, Propylene Glycol, Isopropyl Myristate, Aloe Barbadensis Leaf Juice, Tocopheryl Acetate (Vitamin E), Carbomer, Aminomethyl Propanol

QUESTIONS

www.zep.com